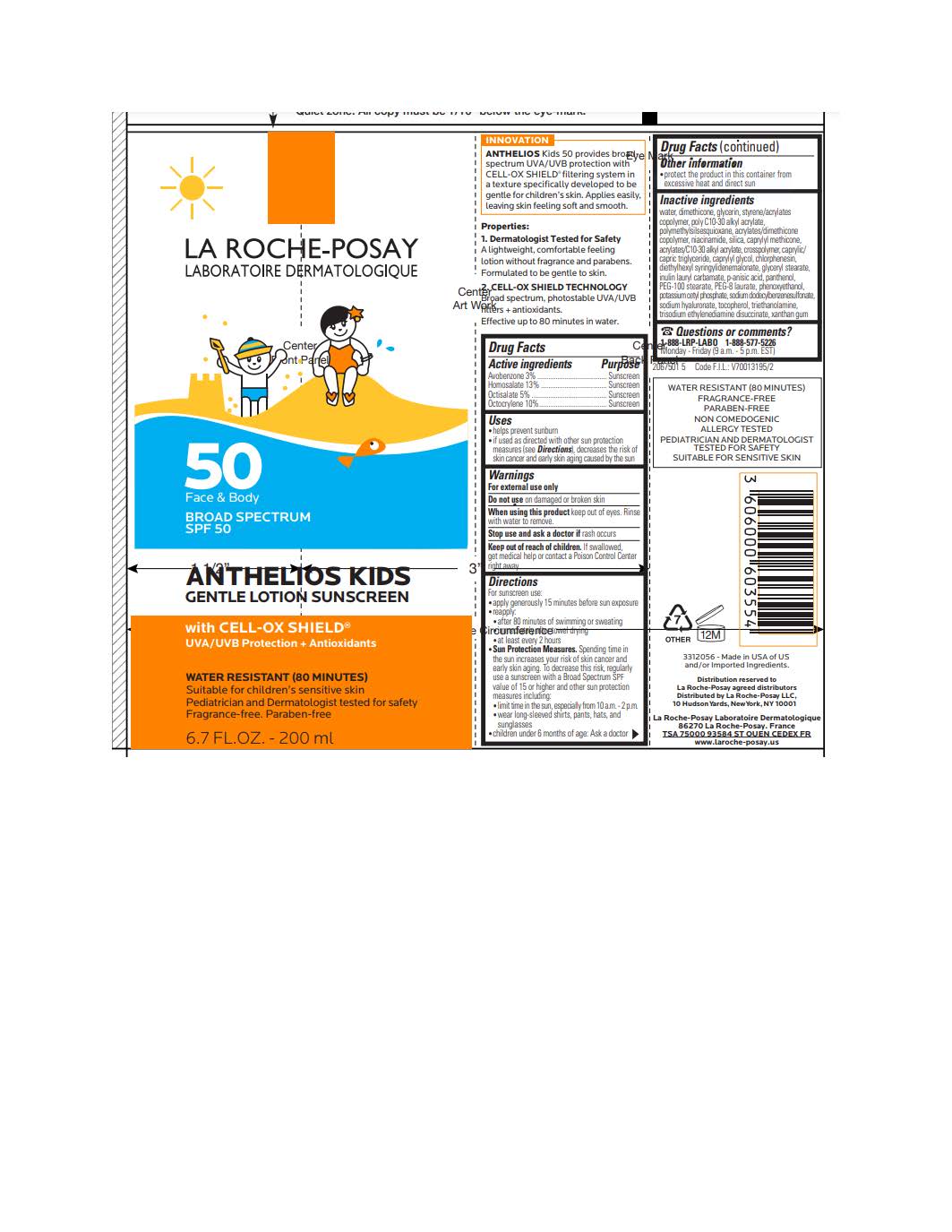 DRUG LABEL: La Roche Posay Laboratoire Dermatologique Anthelios Kids Gentle Broad Spectrum SPF 50 Sunscreen for Face and Body Water Resistant 80 Minutes
NDC: 49967-603 | Form: LOTION
Manufacturer: L'Oreal USA Products Inc
Category: otc | Type: HUMAN OTC DRUG LABEL
Date: 20240101

ACTIVE INGREDIENTS: AVOBENZONE 30 mg/1 mL; HOMOSALATE 130 mg/1 mL; OCTISALATE 50 mg/1 mL; OCTOCRYLENE 100 mg/1 mL
INACTIVE INGREDIENTS: WATER; DIMETHICONE; GLYCERIN; CYCLOMETHICONE 6; POLYMETHYLSILSESQUIOXANE (4.5 MICRONS); NIACINAMIDE; SILICON DIOXIDE; CAPRYLYL TRISILOXANE; MEDIUM-CHAIN TRIGLYCERIDES; CAPRYLYL GLYCOL; CHLORPHENESIN; DIETHYLHEXYL SYRINGYLIDENEMALONATE; GLYCERYL DISTEARATE; INULIN LAURYL CARBAMATE; P-ANISIC ACID; PANTHENOL; PEG-100 STEARATE; PEG-8 LAURATE; PHENOXYETHANOL; POTASSIUM CETYL PHOSPHATE; SODIUM DODECYLBENZENESULFONATE; HYALURONATE SODIUM; TOCOPHEROL; TROLAMINE; TRISODIUM ETHYLENEDIAMINE DISUCCINATE; XANTHAN GUM

Drug Facts

Active ingredient

Avobenzone 3%

Homosalate 13%

Octisalate 5%

Octocrylene 10%

Purpose

Sunscreen

Uses

- helps prevent sunburn
- if used as directed with other sun protection measures (see Directions), decreases the risk of skin cancer and early skin aging caused by the sun

Warnings

For external use only

Do not use

on damaged or broken skin

When using this product

keep out of eyes. Rinse with water to remove.

Stop use and ask a doctor if

rash occurs

Keep out of reach of children.

If swallowed, get medical help or contact a Poison Control Center right away.

Directions

For sunscreen use:

● apply generously 15 minutes before sun exposure

● reapply:

● after 80 minutes of swimming or sweating

● immediately after towel drying

● at least every 2 hours

● Sun Protection Measures. Spending time in the sun increases your risk of skin cancer and early skin aging. To decrease this risk, regularly use a sunscreen with a Broad Spectrum SPF value of 15 or higher and other sun protection measures including:

● limit time in the sun, especially from 10 a.m. – 2 p.m.

● wear long-sleeved shirts, pants, hats, and sunglasses

● children under 6 months of age: Ask a doctor

Other information

protect the product in this container from excessive heat and direct sun

Inactive ingredients

water, dimethicone, glycerin, styrene/acrylates copolymer, poly c10-30 alkyl acrylate, polymethylsilsesquioxane, acrylates/dimethicone copolymer, niacinamide, silica, caprylyl methicone, acrylates/c10-30 alkyl acrylate crosspolymer, caprylic/capric triglyceride, caprylyl glycol, chlorphenesin, diethylhexyl syringylidenemalonate, glyceryl stearate, inulin lauryl carbamate, p-anisic acid, panthenol, PEG-100 stearate, PEG-8 laurate, phenoxyethanol, potassium cetyl phosphate, sodium dodecylbenzenesulfonate, sodium hyaluronate, tocopherol, triethanolamine, trisodium ethylenediamine disuccinate, xanthan gum

Questions or comments?

1-888-LRP-LABO 1-888-577-5226

Monday - Friday (9 a.m. - 5 p.m. EST)